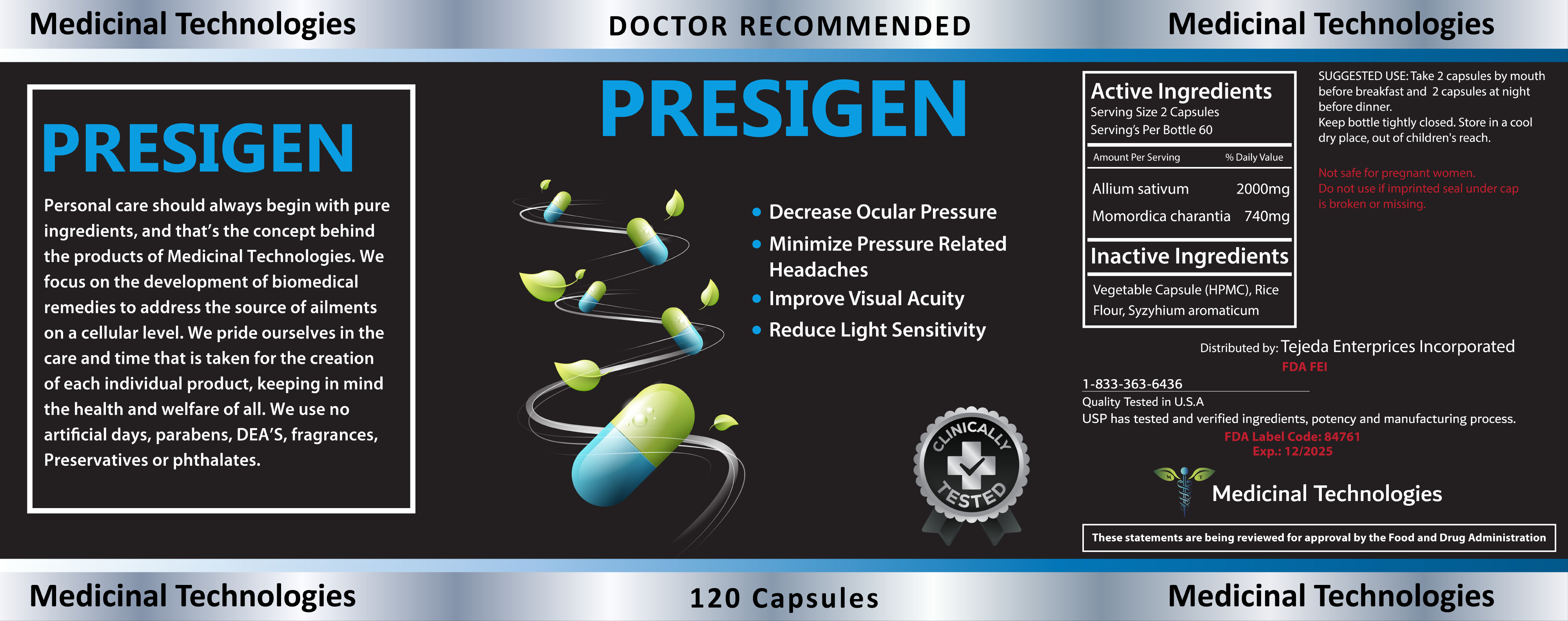 DRUG LABEL: PRESIGEN
NDC: 84761-0003 | Form: CAPSULE
Manufacturer: Tejeda Enterprises Incorporated
Category: otc | Type: HUMAN OTC DRUG LABEL
Date: 20251228

ACTIVE INGREDIENTS: ALLIUM SATIVUM WHOLE 2000 mg/2 U; MOMORDICA CHARANTIA STEM 740 mg/2 U
INACTIVE INGREDIENTS: SYZYGIUM AROMATICUM LEAF

DOSAGE AND ADMINISTRATION

SUGGESTED USE: Take 2 capsules by mouth before breakfast and 2 capsules at night before dinner.

WARNINGS

Keep bottle tightly closed. Store in a cool dry place, out of children's reach.

Not safe for pregnant women,

Do not use if imprinted seal under cap is broken or missing.

Inactive Ingredients
Vegetable Capsule (HPMC), Rice Flour, Syzygium aromaticum L

INDICATIONS AND USAGE

Medicinal Technologies
PRESIGEN
Personal care should always begin with pure ingredients, and that's the concept behind the products of Medicinal Technologies. We focus on the development of biomedical remedies to address the source of ailments on a cellular level. We pride ourselves in the care and time that is taken for the creation of each individual product, keeping in mind the health and welfare of all. We use no artificial days, parabens, DEA'S, fragrances, Preservatives or phthalates.
Medicinal Technologies
DOCTOR RECOMMENDED
PRESIGEN
Decrease Ocular Pressure
Minimize Pressure Related Headaches
Improve Visual Acuity• Reduce Light Sensitivity

ACTIVE INGREDIENT

Allium sativum

Momordica charantia

KEEP OUT OF REACH OF CHILDREN

Keep bottle tightly closed. Store in a cool dry place, out of children's reach.

PURPOSE

Minimize Pressure Related Headaches
Improve Visual Acuity
Reduce Light Sensitivity

PACKAGE LABEL

Medicinal Technologies
PRESIGEN

Content of Labeling